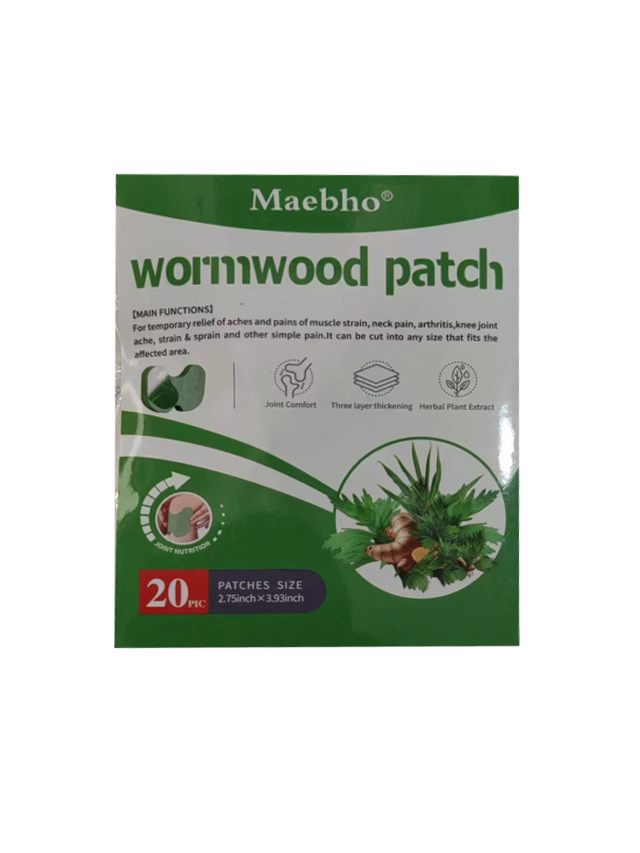 DRUG LABEL: wormwood patch
NDC: 84727-013 | Form: PATCH
Manufacturer: Guangzhou Baishili Trading Co., Ltd
Category: otc | Type: HUMAN OTC DRUG LABEL
Date: 20241027

ACTIVE INGREDIENTS: WORMWOOD 0.4 g/0.4 g; SAFFLOWER 0.4 g/0.4 g; GINGER 0.4 g/0.4 g
INACTIVE INGREDIENTS: CAPSICUM 0.4 g/0.4 g

Health care function

Relieve neck, shoulder, waist, leg pain and promote health

USage

Opened the package back lining paper torn off，clean your skin where the discomfort,aim at the knee or discomfort parts were applied，the corresponding around six to eight hours per post.

Matters needing attention

1. The skin lesions were banned, allergic to wormwood careful.

2. During the period of a few people use local have tickling feeling or a red rash,does not afect theuse disappeared gradually after stopping

3. The use of skin burns is a normal phenomenon.

Unsuitable people

Pregnant women, those allergic to wormwood are prohibited

Keep out of reach of children.

If swallowed, get medical help or contact a Poison Control Center right away

DOSAGE & ADMINISTRATION SECTION

Apply one piece at a time, and each piece should be applied for 8 hours

INACTIVE INGREDIENT SECTION

Peppermint 50%

DOSAGE AND ADMINISTRATION

Medical glue 40%

Far infrared ceramic powder 5%

Magnetic Powder 5%